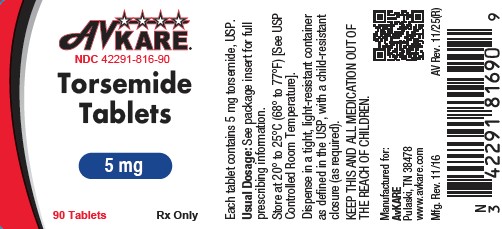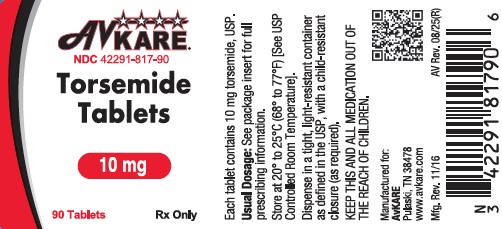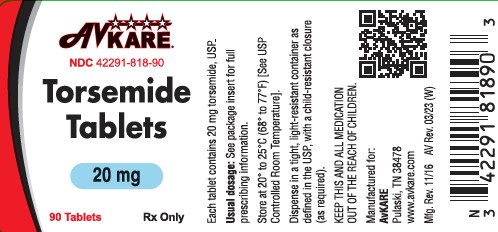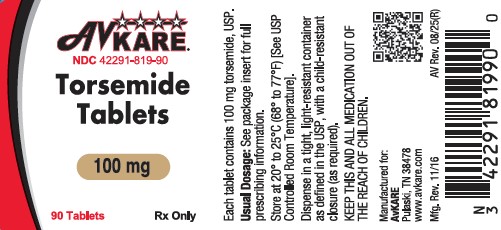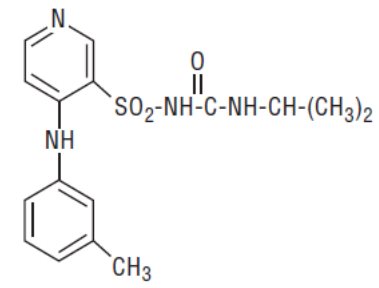 DRUG LABEL: Torsemide
NDC: 42291-819 | Form: TABLET
Manufacturer: AvKARE
Category: prescription | Type: HUMAN PRESCRIPTION DRUG LABEL
Date: 20260211

ACTIVE INGREDIENTS: TORSEMIDE 100 mg/1 1
INACTIVE INGREDIENTS: SILICON DIOXIDE; STARCH, CORN; LACTOSE MONOHYDRATE; MAGNESIUM STEARATE; SODIUM STARCH GLYCOLATE TYPE A POTATO

HIGHLIGHTS OF PRESCRIBING INFORMATION

Torsemide Tablets
These highlights do not include all the information needed to use TORSEMIDE TABLETS safely and effectively. See full prescribing information for TORSEMIDE TABLETS.
TORSEMIDE tablets, for oral use
Initial U.S. Approval: 1993

1 INDICATIONS AND USAGE

Torsemide tablets are a loop diuretic indicated for:

- the treatment of edema associated with heart failure, renal disease or hepatic disease. (1.1)
- the treatment of hypertension, to lower blood pressure. Lowering blood pressure reduces the risk of fatal and nonfatal cardiovascular events, primarily strokes and myocardial infarctions. (1.2)

2 DOSAGE AND ADMINISTRATION

Edema associated with:

- Heart failure: Initial dose is 10 or 20 mg once daily. Titrate by factors of two; doses above 200 mg have not been studied. (2.1)
- Chronic Renal Failure: Initial dose is 20 mg once daily. Titrate by factors of two; doses above 200 mg have not been studied. (2.1)
- Hepatic Cirrhosis: Initial dose is 5 or 10 mg once daily. Titrate by factors of two; doses above 40 mg have not been studied. (2.1)

Hypertension:

- The recommended initial dose is 5 mg once daily. After 4 to 6 weeks, increase to 10 mg once daily, if needed. If 10 mg is insufficient, consider adding another agent. (2.2)

3 DOSAGE FORMS AND STRENGTHS

Tablets: 5 mg, 10 mg, 20 mg and 100 mg (3)

4 CONTRAINDICATIONS

Hypersensitivity to torsemide, anuria, and hepatic coma. (4)

5 WARNINGS AND PRECAUTIONS

- Hypotension and worsening renal function: monitor volume status and renal function periodically (5.1)
- Electrolyte and metabolic abnormalities: monitor serum electrolytes and blood glucose periodically. (5.2)
- Ototoxicity (5.3, 7.6)

6 ADVERSE REACTIONS

The most common adverse reaction is excessive urination (6.7%). (6.1)

To report SUSPECTED ADVERSE REACTIONS, contact AvKARE at 1-855-361-3993 or FDA at 1-800-FDA-1088 or www.fda.gov/medwatch.

7 DRUG INTERACTIONS

- Non-steroidal anti-inflammatory drugs (NSAIDs): Reduced diuretic, natriuretic, and antihypertensive effects; risk of renal impairment. (7.1)
- CYP2C9: Concomitant use with CYP2C9 inhibitors can decrease torsemide clearance. Torsemide may affect the efficacy and safety of sensitive CYP2C9 substrates or of substrates with a narrow therapeutic range, such as warfarin or phenytoin. (7.2)
- Cholestyramine: Decreased exposure of torsemide.(7.3)
- Organic anion drugs: may decrease diuretic activity of torsemide. (7.4)
- Lithium: Risk of lithium toxicity (7.5)
- Renin-angiotensin inhibitors: Increased risk of hypotension and renal impairment. (7.7)
- Radiocontrast agents: Increased risk of renal toxicity. (7.8)
- Corticosteroids and ACTH: Increased risk of hypokalemia. (7.9)

FULL PRESCRIBING INFORMATION

1 INDICATIONS AND USAGE

1.1 Edema

Torsemide tablets are indicated for the treatment of edema associated with heart failure, renal disease or hepatic disease.

1.2 Hypertension

Torsemide tablets are indicated for the treatment of hypertension, to lower blood pressure. Lowering blood pressure reduces the risk of fatal and nonfatal cardiovascular events, primarily strokes and myocardial infarctions. These benefits have been seen in controlled trials of antihypertensive drugs from a wide variety of pharmacologic classes including the class to which this drug principally belongs. There are no controlled trials demonstrating risk reduction with torsemide.

Control of high blood pressure should be part of comprehensive cardiovascular risk management, including, as appropriate, lipid control, diabetes management, antithrombotic therapy, smoking cessation, exercise, and limited sodium intake. Many patients will require more than one drug to achieve blood pressure goals. For specific advice on goals and management, see published guidelines, such as those of the National High Blood Pressure Education Program’s Joint National Committee on Prevention, Detection, Evaluation, and Treatment of High Blood Pressure (JNC).

Numerous antihypertensive drugs, from a variety of pharmacologic classes and with different mechanisms of action, have been shown in randomized controlled trials to reduce cardiovascular morbidity and mortality, and it can be concluded that it is blood pressure reduction, and not some other pharmacologic property of the drugs, that is largely responsible for those benefits. The largest and most consistent cardiovascular outcome benefit has been a reduction in the risk of stroke, but reductions in myocardial infarction and cardiovascular mortality also have been seen regularly.

Elevated systolic or diastolic pressure causes increased cardiovascular risk, and the absolute risk increase per mmHg is greater at higher blood pressures, so that even modest reductions of severe hypertension can provide substantial benefit. Relative risk reduction from blood pressure reduction is similar across populations with varying absolute risk, so the absolute benefit is greater in patients who are at higher risk independent of their hypertension (for example, patients with diabetes or hyperlipidemia), and such patients would be expected to benefit from more aggressive treatment to a lower blood pressure goal.

The antihypertensive effects of torsemide are on the average greater in black patients than in nonblack patients [see Clinical Pharmacology (12.2)] . Some antihypertensive drugs have smaller blood pressure effects (as monotherapy) in black patients, and many antihypertensive drugs have additional approved indications and effects (e.g., on angina, heart failure, or diabetic kidney disease). These considerations may guide selection of therapy.

Torsemide can be used alone or in combination with other antihypertensive agents.

2 DOSAGE AND ADMINISTRATION

2.1 Treatment of Edema

Edema associated with heart failure

The recommended initial dose is 10 mg or 20 mg oral torsemide tablets once daily. If the diuretic response is inadequate, titrate upward by approximately doubling until the desired diuretic response is obtained. Doses higher than 200 mg have not been adequately studied.

Edema associated with chronic renal failure

The recommended initial dose is 20 mg oral torsemide tablets once daily. If the diuretic response is inadequate, titrate upward by approximately doubling until the desired diuretic response is obtained. Doses higher than 200 mg have not been adequately studied.

Edema associated with hepatic cirrhosis

The recommended initial dose is 5 mg or 10 mg oral torsemide tablets once daily, administered together with an aldosterone antagonist or a potassium-sparing diuretic. If the diuretic response is inadequate, titrate upward by approximately doubling until the desired diuretic response is obtained. Doses higher than 40 mg have not been adequately studied in this population.

2.2 Treatment of Hypertension

The recommended initial dose is 5 mg once daily. If the 5 mg dose does not provide adequate reduction in blood pressure within 4 to 6 weeks, increase to 10 mg once daily. If the response to 10 mg is insufficient, add another antihypertensive agent to the treatment regimen.

3 DOSAGE FORMS AND STRENGTHS

Torsemide Tablets are available as white to off white scored tablets in 5-, 10-, 20-, and 100-mg strengths.

4 CONTRAINDICATIONS

Torsemide is contraindicated in patients with known hypersensitivity to torsemide.

Torsemide is contraindicated in patients who are anuric.

Torsemide is contraindicated in patients with hepatic coma.

5 WARNINGS AND PRECAUTIONS

5.1 Hypotension and Worsening Renal Function

Excessive diuresis may cause potentially symptomatic dehydration, blood volume reduction and hypotension and worsening renal function, including acute renal failure particularly in salt-depleted patients or those taking renin-angiotensin aldosterone inhibitors. Worsening of renal function can also occur with concomitant use of nephrotoxic drugs (e.g., aminoglycosides, cisplatin, and NSAIDs). Monitor volume status and renal function periodically.

5.2 Electrolyte and Metabolic Abnormalities

Torsemide can cause potentially symptomatic hypokalemia, hyponatremia, hypomagnesemia, hypocalcemia, and hypochloremic alkalosis. Treatment with torsemide can cause an increase in blood glucose levels and hyperglycemia. Asymptomatic hyperuricemia can occur and gout may rarely be precipitated. Monitor serum electrolytes and blood glucose periodically.

5.3 Ototoxicity

Tinnitus and hearing loss (usually reversible) have been observed with loop diuretics, including torsemide. Higher than recommended doses, severe renal impairment, and hypoproteinemia, appear to increase the risk of ototoxicity.

6 ADVERSE REACTIONS

The following risks are discussed in more detail in other sections:

- Hypotension and Worsening Renal Function [see Warnings and Precautions (5.1)]
- Electrolyte and Metabolic Abnormalities [see Warnings and Precautions (5.2)]
- Ototoxicity [see Warnings and Precautions (5.3)]

6.1 Clinical Trials Experience

Because clinical trials are conducted under widely varying conditions, adverse reaction rates observed in the clinical trials of a drug cannot be directly compared to rates in the clinical trials of another drug and may not reflect the rates observed in practice.

In pre-approval studies, torsemide has been evaluated for safety in approximately 4000 subjects; over 800 of these subjects received torsemide for at least 6 months, and over 380 were treated for more than 1 year. Among these subjects were 564 who received torsemide during United States-based trials in which 274 other subjects received placebo.

Discontinuation of therapy due to adverse reactions occurred in 3.5% of United States patients treated with torsemide and in 4.4% of patients treated with placebo.

In United States placebo-controlled trials excessive urination occurred in 6.7% of patients compared with 2.2% of patients receiving placebo. The daily doses of torsemide used in these trials ranged from 1.25 mg to 20 mg, with most patients receiving 5 mg to 10 mg; the duration of treatment ranged from 1 to 52 days, with a median of 41 days.

In the placebo-controlled hypertension studies excessive urination was dose related; 1% of patients receiving placebo, 4% of those treated with 5 mg of daily torsemide, and 15% of those treated with 10 mg. Excessive urination was generally not reported as an adverse event among patients who received torsemide for cardiac, renal, or hepatic failure.

There was no effect of age or sex on the incidence of adverse reactions.

Laboratory Parameters

Potassium

In controlled studies in the United States, torsemide was administered to hypertensive patients at doses of 5 mg or 10 mg daily. After 6 weeks at these doses, the mean decrease in serum potassium was approximately 0.1 mEq/L. The percentage of patients who had a serum potassium level below 3.5 mEq/L at any time during the studies was 1.5% on torsemide and 3% on placebo. In patients followed for 1 year, there was no progressive change in mean serum potassium levels. In patients with congestive heart failure, hepatic cirrhosis, or renal disease treated with torsemide at doses higher than those studied in United States antihypertensive trials, hypokalemia was observed with greater frequency, in a dose-related manner.

Blood Urea Nitrogen (BUN), Creatinine and Uric Acid

Torsemide produces small dose-related increases in each of these laboratory values. In hypertensive patients who received 10 mg of torsemide daily for 6 weeks, the mean increase in blood urea nitrogen was 1.8 mg/dL (0.6 mmol/L), the mean increase in serum creatinine was 0.05 mg/dL (4 mmol/L), and the mean increase in serum uric acid was 1.2 mg/dL (70 mmol/L). Little further change occurred with long-term treatment, and all changes reversed when treatment was discontinued.

Glucose

Hypertensive patients who received 10 mg of daily torsemide experienced a mean increase in serum glucose concentration of 5.5 mg/dL (0.3 mmol/L) after 6 weeks of therapy, with a further increase of 1.8 mg/dL (0.1 mmol/L) during the subsequent year. In long-term studies in diabetics, mean fasting glucose values were not significantly changed from baseline.

Serum Lipids

Torsemide 20 mg caused small increases in total cholesterol and triglycerides in short term hypertension studies. The changes subsided with chronic therapy.

6.2 Postmarketing Experience

The following adverse reactions have been identified during the post-approval use of torsemide. Because these reactions are reported voluntarily from a population of uncertain size, it is not always possible to estimate their frequency reliably or establish a causal relationship to drug exposure.

Gastrointestinal system: Pancreatitis, abdominal pain

Nervous System: Paresthesia, confusion, visual impairment, loss of appetite

Hematologic: Leucopenia, thrombocytopenia, anemia

Hepatobiliary: Increase in liver transaminases, gamma-glutamyltransferase

Metabolism: Thiamine (vitamin B1) deficiency

Skin/hypersensitivity: Stevens-Johnson syndrome, toxic epidermal necrolysis, photosensitivity reaction, pruritus Urogenital: Acute urinary retention

To report SUSPECTED ADVERSE REACTIONS contact AvKARE at 1-855-361-3993; email drugsafety@avkare.com; or
FDA at 1-800-FDA-1088 or www.fda.gov/medwatch.

7 DRUG INTERACTIONS

7.1 Nonsteroidal Anti-inflammatory Drugs

Because torsemide and salicylates compete for secretion by renal tubules, patients receiving high doses of salicylates may experience salicylate toxicity when torsemide is concomitantly administered.

Concomitant use of nonsteroidal anti-inflammatory drugs (NSAIDs) and torsemide has been associated with the development of acute renal failure. The antihypertensive and diuretic effects of torsemide can be reduced by NSAIDs.

Partial inhibition of the natriuretic effect of torsemide by concomitant administration of indomethacin has been demonstrated for torsemide under conditions of dietary sodium restriction (50 mEq/day) but not in the presence of normal sodium intake (150 mEq/day).

7.2 Cytochrome P450 2C9 Inhibitors and Inducers

Torsemide is a substrate of CYP2C9. Concomitant use of CYP2C9 inhibitors (e.g., amiodarone, fluconazole, miconazole, oxandrolone) can decrease torsemide clearance and increase torsemide plasma concentrations. Concomitant use of CYP2C9 inducers (e.g., rifampin) increase torsemide clearance and decrease plasma torsemide concentrations. Monitor diuretic effect and blood pressure when used in combination with CYP2C9 inhibitor or inducer. Adjust torsemide dose if necessary.

Because of its inhibition of CYP2C9 metabolism, torsemide may affect the efficacy and safety of sensitive CYP2C9 substrates, such as celecoxib, or of substrates with a narrow therapeutic range, such as warfarin or phenytoin. Monitor patients and adjust dosages if necessary.

7.3 Cholestyramine

Concomitant use of torsemide and cholestyramine has not been studied in humans but, in a study in animals, coadministration of cholestyramine decreased the absorption of orally administered torsemide. If torsemide and cholestyramine should be coadministered, administer torsemide at least one hour before or 4 to 6 h after cholestyramine administration.

7.4 Organic Anion Drugs

Coadministration of organic anion drugs (e.g., probenecid) that undergo significant renal tubular secretion have the potential to reduce secretion of torsemide into the proximal tubule and thereby decreases the diuretic activity of torsemide. Monitor diuretic effect and blood pressure during coadministration.

7.5 Lithium

Like other diuretics, torsemide reduces the renal clearance of lithium, inducing a high risk of lithium toxicity. Monitor lithium levels periodically when torsemide is coadministered.

7.6 Ototoxic Drugs

Loop diuretics increase the ototoxic potential of other ototoxic drugs, including aminoglycoside antibiotics and ethacrynic acid. This effect has been reported with concomitant use of torsemide and gentamycin. Avoid concomitant use of torsemide and aminoglycoside antibiotics, if possible.

7.7 Renin-angiotensin Inhibitors

Coadministration of torsemide with ACE inhibitors or angiotensin receptor blockers can increase the risk of hypotension and renal impairment.

7.8 Radiocontrast Agents

Torsemide can increase the risk of renal toxicity related to administration of radiocontrast agents.

7.9 Corticosteroids and ACTH

Concomitant use with torsemide may increase risk of hypokalemia.

8 USE IN SPECIFIC POPULATIONS

8.1 Pregnancy

Risk Summary

There are no available data on use of torsemide in pregnant women and the risk of major birth defects or miscarriage. In pregnant rats and rabbits dosed, on a mg/m^2 basis, with 10 and 1.7 times a human dose of 20 mg/day, respectively, there was no fetotoxicity or teratogenicity. However, in pregnant rats and rabbits administered 50 and 6.8 times the human dose, respectively, decreases in body weight, decreased fetal resorption and delayed fetal ossification was observed.

The estimated background risk of major birth defects and miscarriage for the indicated population is unknown. All pregnancies have a background risk of birth defect, loss, or other adverse outcomes. In the U.S. general population, the estimated background risk of major malformations and miscarriage in clinically recognized pregnancies is 2 to 4%, and 15 to 20%, respectively.

Data

There was no fetotoxicity or teratogenicity in rats treated with up to 5 mg/kg/day of torsemide (on a mg/kg basis, this is 15 times a human dose of 20 mg/day; on a mg/m^2 basis, the animal dose is 10 times the human dose), or in rabbits, treated with 1.6 mg/kg/day (on a mg/kg basis, 5 times the human dose of 20 mg/kg/day; on a mg/m^2 basis, 1.7 times this dose). Fetal and maternal toxicity (decrease in average body weight, increase in fetal resorption and delayed fetal ossification) occurred in rabbits and rats given doses 4 (rabbits) and 5 (rats) times larger.

8.2 Lactation

Risk Summary

There are no data regarding the presence of torsemide in human milk or the effects of torsemide on the breastfed child. Diuretics can suppress lactation.

8.4 Pediatric Use

Safety and effectiveness in pediatric patients have not been established.

Administration of another loop diuretic to premature infants has been associated with the precipitation of nephrocalcinosis/nephrolithiasis. Nephrocalcinosis/nephrolithiasis has also been observed in children under 4 years of age with no history of prematurity who have been treated chronically with the other loop diuretic. The other loop diuretic, when administered during the first weeks of life, has also been reported to increase the risk of persistent patent ductus arteriosus. The use of torsemide in such patients has not been studied.

8.5 Geriatric Use

Of the total number of patients who received torsemide in United States clinical studies, 24% were 65 or older while about 4% were 75 or older. No specific age-related differences in effectiveness or safety were observed between younger patients and elderly patients.

8.6 Use in Renal Impairment

In single-dose studies in patients with non-anuric renal failure, high doses of torsemide (20 mg to 200 mg) caused marked increases in water and sodium excretion. In patients with non-anuric renal failure, severe enough to require hemodialysis, chronic treatment with up to 200 mg of daily torsemide has not been shown to change steady-state fluid retention. When patients in a study of acute renal failure received total daily doses of 520 mg to 1200 mg of torsemide, 19% experienced seizures. Ninety-six patients were treated in this study; 6/32 treated with torsemide experienced seizures, 6/32 treated with comparably high doses of furosemide experienced seizures, and 1/32 treated with placebo experienced a seizure.

8.7 Use in Hepatic Impairment

Torsemide can cause sudden alterations of fluid and electrolyte balance which may precipitate hepatic coma in patients with hepatic disease with cirrhosis and ascites. In these patients, diuresis with torsemide is best initiated in the hospital.

Diuretic treatment can cause or contribute to the development of hypovolemia, hypokalemia, metabolic alkalosis, hyponatremia or azotemia which can lead to new or worsening hepatic encephalopathy. Consider suspending or discontinuing torsemide [see Contraindications (4)].

To prevent hypokalemia and metabolic alkalosis, use an aldosterone antagonist or potassium-sparing drug with torsemide in patients with hepatic disease.

When given with aldosterone antagonists, torsemide also caused increases in sodium and fluid excretion in patients with edema or ascites due to hepatic cirrhosis. Urinary sodium excretion rate relative to the urinary excretion rate of torsemide is less in cirrhotic patients than in healthy subjects (possibly because of the hyperaldosteronism and resultant sodium retention that are characteristic of portal hypertension and ascites). However, because of the increased renal clearance of torsemide in patients with hepatic cirrhosis, these factors tend to balance each other, and the result is an overall natriuretic response that is similar to that seen in healthy subjects. Chronic use of any diuretic in hepatic disease has not been studied in adequate and well-controlled trials.

10 OVERDOSE

The signs and symptoms of overdosage can be anticipated to include those of excessive pharmacologic effect: dehydration, hypovolemia, hypotension, hyponatremia, hypokalemia, hypochloremic alkalosis, and hemoconcentration. Treatment of overdosage should consist of fluid and electrolyte replacement.

Laboratory determinations of serum levels of torsemide and its metabolites are not widely available.

No data are available to suggest physiological maneuvers (e.g., maneuvers to change the pH of the urine) that might accelerate elimination of torsemide and its metabolites. Torsemide is not dialyzable, so hemodialysis will not accelerate elimination.

11 DESCRIPTION

Torsemide, USP is a diuretic of the pyridine-sulfonylurea class. Its chemical name is 1-isopropyl-3-[(4- m-toluidino-3-pyridyl) sulfonyl] urea and its structural formula is:

C16H20N4O3S M.W. 348.43

Its pKa is 7.1.

Torsemide, USP is a white to off-white crystalline powder. Each Torsemide Tablet for oral administration contains 5 mg, 10 mg, 20 mg or 100 mg of torsemide, USP. In addition, each tablet contains the following inactive ingredients: colloidal silicon dioxide, corn starch, lactose monohydrate, magnesium stearate and sodium starch glycolate.

12 CLINICAL PHARMACOLOGY

12.1 Mechanism of Action

Micropuncture studies in animals have shown that torsemide acts from within the lumen of the thick ascending portion of the loop of Henle, where it inhibits the Na^+/K^+/2Cl^–-carrier system. Clinical pharmacology studies have confirmed this site of action in humans, and effects in other segments of the nephron have not been demonstrated. Diuretic activity thus correlates better with the rate of drug excretion in the urine than with the concentration in the blood.

Torsemide increases the urinary excretion of sodium, chloride, and water, but it does not significantly alter glomerular filtration rate, renal plasma flow, or acid-base balance.

12.2 Pharmacodynamics

With oral dosing, the onset of diuresis occurs within 1 hour and the peak effect occurs during the first or second hour and diuresis lasts about 6 to 8 hours. In healthy subjects given single doses, the dose-response relationship for sodium excretion is linear over the dose range of 2.5 mg to 20 mg. The increase in potassium excretion is negligible after a single dose of up to 10 mg and only slight (5 mEq to 15 mEq) after a single dose of 20 mg.

Edema

Torsemide has been studied in controlled trials in patients with New York Heart Association Class II to Class IV heart failure. Patients who received 10 mg to 20 mg of daily torsemide in these studies achieved significantly greater reductions in weight and edema than did patients who received placebo.

Hypertension

In patients with essential hypertension, torsemide has been shown in controlled studies to lower blood pressure when administered once a day at doses of 5 mg to 10 mg. The antihypertensive effect is near maximal after 4 to 6 weeks of treatment, but it may continue to increase for up to 12 weeks. Systolic and diastolic supine and standing blood pressures are all reduced. There is no significant orthostatic effect, and there is only a minimal peak-trough difference in blood pressure reduction.

The antihypertensive effects of torsemide are, like those of other diuretics, on the average greater in black patients (a low-renin population) than in nonblack patients.

When torsemide is first administered, daily urinary sodium excretion increases for at least a week. With chronic administration, however, daily sodium loss comes into balance with dietary sodium intake. If the administration of torsemide is suddenly stopped, blood pressure returns to pretreatment levels over several days, without overshoot.

Torsemide has been administered together with β-adrenergic blocking agents, ACE inhibitors, and calcium-channel blockers. Adverse drug interactions have not been observed, and special dosage adjustment has not been necessary.

12.3 Pharmacokinetics

Absorption

The bioavailability of torsemide tablets is approximately 80%, with small inter-subject variation; the 90% confidence interval is 75% to 89%. The drug is absorbed with little first-pass metabolism, and the serum concentration reaches its peak (Cmax) within 1 hour after oral administration. Cmax and area under the serum concentration-time curve (AUC) after oral administration are proportional to dose over the range of 2.5 mg to 200 mg. Simultaneous food intake delays the time to Cmax by about 30 minutes, but overall bioavailability (AUC) and diuretic activity are unchanged.

Distribution

The volume of distribution of torsemide is 12 to 15 liters in normal adults or in patients with mild to moderate renal failure or congestive heart failure. In patients with hepatic cirrhosis, the volume of distribution is approximately doubled. Torsemide is extensively bound to plasma protein (>99%).

Metabolism

Torsemide is metabolized by the hepatic cytochrome CYP2C9 and, to a minor extent, CYP2C8 and CYP2C18. Three main metabolites have been identified in humans. Metabolite M1 is formed by methyl-hydroxylation of torsemide, metabolite M3 is formed by ring hydroxylation of torsemide, and metabolite M5 is formed by oxidation of M1. The major metabolite in humans is the carboxylic acid derivative M5, which is biologically inactive. Metabolites M1 and M3 possess some pharmacological activity; however, their systemic exposures are much lower when compared to torsemide.

Elimination

In normal subjects the elimination half-life of torsemide is approximately 3.5 hours. Torsemide is cleared from the circulation by both hepatic metabolism (approximately 80% of total clearance) and excretion into the urine (approximately 20% of total clearance in patients with normal renal function).

Because torsemide is extensively bound to plasma protein (>99%), very little enters tubular urine via glomerular filtration. Most renal clearance of torsemide occurs via active secretion of the drug by the proximal tubules into tubular urine.

After a single oral dose, the amounts recovered in urine were: torsemide 21%, metabolite M1 12%, metabolite M3 2%, and metabolite M5 34%.

Renal Impairment

In patients with renal failure, renal clearance of torsemide is markedly decreased but total plasma clearance is not significantly altered. A smaller fraction of the administered dose is delivered to the intraluminal site of action, and the natriuretic action of any given dose of diuretic is reduced.

Hepatic Impairment

In patients with hepatic cirrhosis, the volume of distribution, plasma half-life, and renal clearance are all increased, but total clearance is unchanged.

Geriatric Patients

The renal clearance of torsemide is lower in elderly subjects as compared to younger adults, which is related to the decline in renal function that commonly occurs with aging. However, total plasma clearance and elimination half-life remain unchanged.

Heart failure

In patients with decompensated congestive heart failure, hepatic and renal clearance are both reduced, probably because of hepatic congestion and decreased renal plasma flow, respectively. The total clearance of torsemide is approximately 50% of that seen in healthy volunteers, and the plasma half-life and AUC are correspondingly increased. Because of reduced renal clearance, a smaller fraction of any given dose is delivered to the intraluminal site of action, so at any given dose there is less natriuresis in patients with heart failure than in normal subjects.

Drug Interactions

Digoxin: Coadministration of digoxin is reported to increase the AUC for torsemide by 50%, but dose adjustment of torsemide is not necessary. Torsemide does not affect the pharmacokinetics of digoxin.

Spironolactone: In healthy subjects, coadministration of torsemide was associated with significant reduction in the renal clearance of spironolactone, with corresponding increases in the AUC. However, the pharmacokinetic profile and diuretic activity of torsemide are not altered by spironolactone.

Torsemide does not affect the protein binding of glyburide or warfarin.

Cimetidine: The pharmacokinetic profile and diuretic activity of torsemide are not altered by cimetidine.

13 NONCLINICAL TOXICOLOGY

13.1 Carcinogenesis, Mutagenesis and Impairment of Fertility

No overall increase in tumor incidence was found when torsemide was given to rats and mice throughout their lives at doses up to 9 mg/kg/day (rats) and 32 mg/kg/day (mice). On a body-weight basis, these doses are 27 to 96 times a human dose of 20 mg; on a body-surface-area basis, they are 5 to 8 times this dose. In the rat study, the high-dose female group demonstrated renal tubular injury, interstitial inflammation, and a statistically significant increase in renal adenomas and carcinomas. The tumor incidence in this group was, however, not much higher than the incidence sometimes seen in historical controls. Similar signs of chronic non-neoplastic renal injury have been reported in high-dose animal studies of other diuretics such as furosemide and hydrochlorothiazide.

No mutagenic activity was detected in any of a variety of in vivo and in vitro tests of torsemide and its major human metabolite. The tests included the Ames test in bacteria (with and without metabolic activation), tests for chromosome aberrations and sister-chromatid exchanges in human lymphocytes, tests for various nuclear anomalies in cells found in hamster and murine bone marrow, tests for unscheduled DNA synthesis in mice and rats, and others.

In doses up to 25 mg/kg/day (75 times a human dose of 20 mg on a body-weight basis; 13 times this dose on a body-surface-area basis), torsemide had no adverse effect on the reproductive performance of male or female rats.

16 HOW SUPPLIED/ STORAGE AND HANDLING

Torsemide Tablets are available as follows:

5 mg - White to off white, round, biconvex tablets, debossed with “PA” and “915” on one side and scored on the other side. Available in bottles of 90 (NDC 42291-816-90).

10 mg - White to off white, round, biconvex tablets, debossed with “PA” and “916” on one side and scored on the other side. Available in bottles of 90 (NDC 42291-817-90).

20 mg - White to off white, round, biconvex tablets, debossed with “PA” and “917” on one side and scored on the other side. Available in bottles of 90 (NDC 42291-818-90), in bottles of 100 (NDC 42291-818-01), and in bottles of 500 (NDC 42291-818-50).

100 mg - White to off white, oval, biconvex tablets, debossed with “PA” and “918” on one side and scored on the other side. Available in bottles of 90 (NDC 42291-819-90).

Store at 20° to 25°C (68° to 77°F) [See USP Controlled Room Temperature].

Dispense in a tight, light-resistant container as defined in the USP, with a child-resistant closure (as required).

KEEP THIS AND ALL MEDICATIONS OUT OF THE REACH OF CHILDREN.

17 PATIENT COUNSELING INFORMATION

Symptomatic Hypotension: Advise patients receiving torsemide that lightheadedness can occur, especially during the first days of therapy, and that it should be reported to the prescribing physician. The patients should be told that if syncope occurs, torsemide should be discontinued until the physician has been consulted.

All patients should be cautioned that inadequate fluid intake, excessive perspiration, diarrhea, or vomiting can lead to an excessive fall in blood pressure, with the same consequences of lightheadedness and possible syncope [see Warnings and Precautions (5.1)].

Non-Steroidal Anti-inflammatory Drugs (NSAID): Advise patients to discuss with their physician before taking NSAID medications concomitantly [see Drug Interactions (7.1)] .

Manufactured for:

AvKARE

Pulaski, TN 38478

Mfg. Rev. 02/17

AV Rev. 05/23 (M)